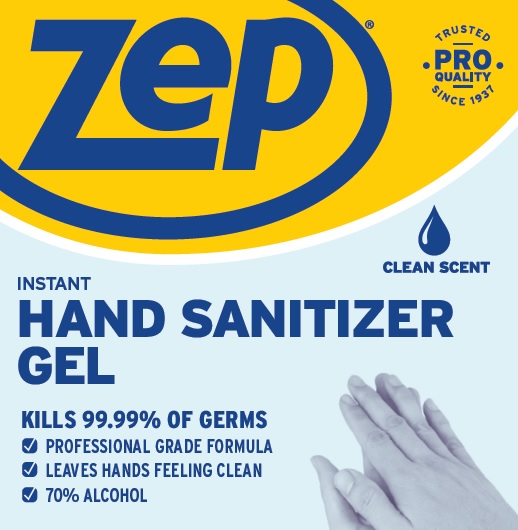 DRUG LABEL: Zep Instant Hand Sanitizer Gel
NDC: 66949-118 | Form: LIQUID
Manufacturer: Zep Inc.
Category: otc | Type: HUMAN OTC DRUG LABEL
Date: 20251226

ACTIVE INGREDIENTS: ALCOHOL 70 mL/100 mL
INACTIVE INGREDIENTS: WATER; POLYETHYLENE GLYCOL 300; ACRYLATES/VINYL ISODECANOATE CROSSPOLYMER (10000 MPA.S NEUTRALIZED AT 0.5%)

66949-118 / IHSG Zep Instant Hand Sanitizer Gel 70%

Active Ingredient

Ethanol 70% v/v

Purpose

Antiseptic

Uses

■ To help reduce germs and bacteria on the skin.
■ Recommended for repeated use.
■ No rinsing required.

Warnings

Flammable. Keep away from fire, flame, or spark. For external use only.

Do not use

in the eye; if in eyes, rinse thoroughly with water.

When using this product

■ Do not swallow.
■ If swallowed, do not induce vomiting and if individual is conscious, give large quantities of water to drink and consult a physician immediately.

Stop use and ask doctor if skin irritation or redness persists for more than 72 hours.

Keep out of reach of children and pets. Children must be supervised in use of this product.

Directions

- Apply gel to hands.
- Rub into hands for at least 20 seconds or until dry.

Other information

■ Keep container closed and stored in a dry area at temperatures between 68°F and 77°F (20°C and 25°C).
■ Do not reuse empty container.
■ Dispose in accordance with all applicable federal, state and local regulations.

Inactive ingredients

Deionized Water, PEG-6 (and) Acrylates/Vinyl Crosspolymer, Fragrance.

Questions or comments?

Call 1-877-I-BUY-ZEP (1-877-428-9937)